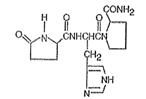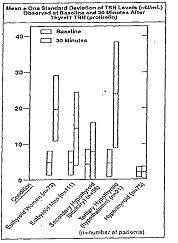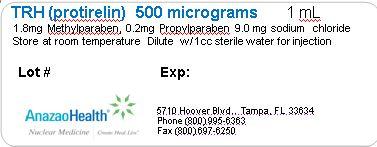 DRUG LABEL: Thyrotropin Releasing Hormone
NDC: 51808-209 | Form: SOLUTION
Manufacturer: AnazaoHealth Corporation
Category: prescription | Type: HUMAN PRESCRIPTION DRUG LABEL
Date: 20120619

ACTIVE INGREDIENTS: PROTIRELIN 500 ug/1 mL
INACTIVE INGREDIENTS: METHYLPARABEN 1.8 mg/1 mL; PROPYLPARABEN 0.2 mg/1 mL; SODIUM CHLORIDE 9 mg/1 mL

Thyrotropin-Releasing Hormone

Dear Medical Professional,

Per your order, we have compounded Thyrotropin-Releasing Hormone (TRH). The characteristics of this preparation are:

DESCRIPTION

Chemically, TRH (protirelin) is identified as 5-oxo-L-prolyl-L-histidyl-L-proline amide. It is a synthetic tripeptide that is believed to be structurally identical to the naturally-occurring thyrotropin-releasing hormone produced by the hypothalamus. The CAS Registry Number is 24305-27-9. The structural formula is:

Figure 1

TRH is supplied as a solution of 1 mL in a 5 mL vial. Each vial contains 500 mcg protirelin, 1.8 mg Methylparaben, 0.2 mg Propylparaben, and 9.0 mg Sodium Chloride. TRH is intended for intravenous administration following dilution with 1 mL sterile water for injection.

CLINICAL PHARMACOLOGY

Pharmacologically, TRH increases the release of the thyroid stimulating hormone (TSH) from the anterior pituitary. Prolactin release is also increased. It has recently been observed that approximately 65% of acromegalic patients tested respond with a rise in circulating growth hormone levels; the clinical significance is as yet not clear. Following intravenous administration, the mean plasma half-life of protirelin in normal subjects is approximately five minutes. TSH levels rise rapidly and reach a peak at 20 to 30 minutes. The decline in TSH levels takes place more slowly, approaching baseline levels after approximately three hours

INDICATIONS AND USAGE

TRH is indicated as an adjunctive agent in the diagnostic assessment of thyroid function. As an adjunct to other diagnostic procedures, testing with TRH (protirelin) may yield useful information in patients with pituitary or hypothalamic dysfunction.

TRH is indicated as an adjunct to evaluate the effectiveness of thyrotropin suppression with a particular dose of T4 in patients with nodular or diffuse goiter. A normal TSH baseline value and a minimal difference between the 30 minute and baseline response to TRH injection would indicate adequate suppression of the pituitary secretion of TSH.

TRH may be used, adjunctively, for adjustment of thyroid hormone dosage given to patients with primary hypothyroidism. A normal or slightly blunted TSH response, thirty minutes following TRH injection, would indicate adequate replacement therapy.

WARNINGS

Transient changes in blood pressure, either increases or decreases, frequently occur immediately following administration of TRH. Blood pressure should therefore be measured before TRH is administered and at frequent intervals during the first 15 minutes after its administration.

Increases in systolic pressure (usually less than 30 mm Hg) and/or increases in diastolic pressure (usually less than 20 mm Hg) have been observed more frequently than decreases in pressure. These changes have not ordinarily persisted for more than 15 minutes nor have they required therapy. More severe degrees of hypertension or hypotension with or without syncope have been reported in a few patients. To minimize the incidence and/or severity of hypotension, the patient should be supine before, during, and after TRH administration. If a clinically important change in blood pressure occurs, monitoring of blood pressure should be continued until it returns to base-line levels.

TRH should not be administered to patients in whom marked, rapid changes in blood pressure would be dangerous unless the potential benefit clearly outweighs the potential risk

PRECAUTIONS

General:

Thyroid hormones reduce the TSH response to TRH. Accordingly, patients in whom TRH is to be used diagnostically should be taken off liothyronine (T3) approximately seven days prior to testing and should be taken off thyroid medications containing levothyroxine (T4), e.g., desiccated thyroid, thyroglobulin, or liotrix, at least 14 days before testing. Hormone therapy is NOT to be discontinued when the test is used to evaluate the effectiveness of thyroid suppression with a particular dose of T4 in patients with nodular or diffuse goiter, or for adjustment of thyroid hormone dosage given to patients with primary hypothyroidism.

Chronic administration of levodopa has been reported to inhibit the TSH response to TRH.

It is not advisable to withdraw maintenance doses of adrenocortical drugs used in the therapy of known hypopituitarism. Several published reports have shown that prolonged treatment with glucocorticoids at physiologic doses has no significant effect on the TSH response to thyrotropin releasing hormone, but that the administration of pharmacologic doses of steroids reduces the TSH response. Therapeutic doses of acetylsalicylic acid (2 to 3.6 g/day) have been reported to inhibit the TSH response to protirelin. The ingestion of acetylsalicylic acid caused the peak level of TSH to decrease approximately 30% as compared to values obtained without acetylsalicylic acid administration. In both cases, the TSH peak occurred 30 minutes post-administration of protirelin.

ADVERSE REACTIONS

Side effects have been reported in about 50% of the patients tested with TRH. Generally, the side effects are moor, have occurred promptly, and have persisted for only a few minutes following injection.

Cardiovascular reactions:

Marked changes in blood pressure, including both hypertension and hypotension with or without syncope, have been reported in a small number of patients.

Endocrine reaction:

Breast enlargement and leakage in lactating women for up to two or three days.

Other reactions:

Headaches, sometimes severe, and transient amaurosis in patients with pituitary tumors. Rarely, convulsions may occur in patients with predisposing conditions, e.g., epilepsy, brain damage. Nausea; urge to urinate; flushed sensation; light-headedness; bad taste in mouth; abdominal discomfort; and dry mouth.

Less frequently reported were:

Anxiety; sweating; tightness in the throat; pressure in the chest; tingling sensation; drowsiness; and allergic reactions.

Pituitary apoplexy requiring acute neurosurgical intervention has been reported infrequently for patients with pituitary macroadenomas following the acute administration of protirelin injection in the setting of combined anterior pituitary function testing in conjunction with LHRH and insulin.

DOSAGE AND ADMINISTRATION

TRH is intended for intravenous administration with the patient in the supine position. The drug is administered as a bolus over a period of 15 to 30 seconds, with the patient remaining supine until all scheduled post injection blood samples have been taken. Blood pressure should be measured before TRH is administered and at frequent intervals during the first 15 minutes thereafter (see WARNINGS). Have the patient urinate before injecting TRH.

Adults: 500 μg. Doses between 200 and 500 μg have been used. 500 μg is considered the optimum dose to give the maximum response in the greatest number of patients. Doses greater than 500 μg are unlikely to elicit a greater TSH response.

Children age 6 to 16 years: 7 μg/kg body weight up to a dose of 500 μg.

Infants and children up to 6 years: Experience is limited in this age group; doses of 7μg/kg have been administered.

One blood sample for TSH assay should be drawn immediately prior to the injection of TRH, and a second sample should be obtained 30 minutes after injection.

The TSH response to TRH is reduced by repetitive administration of the drug. Accordingly, if the TRH test is repeated, an interval of seven days before testing is recommended.

Elevated serum lipids may interfere with the TSH assay. Thus, fasting (except in patients with hypopituitarism) or a low-fat meal is recommended prior to the test.

INTERPRETATION OF TEST RESULTS

Interpretation of the TSH response to TRH requires an understanding of thyroid-pituitary-hypothalamic physiology and knowledge of the clinical status of the individual patient. Because the TSH test results may vary with the laboratory, the physician should be familiar with the TSH assay method used and the normal range for the laboratory performing the assay. TSH response 30 minutes after TRH administration in normal subjects and in patients with hyperthyroidism and hypothyroidism are presented in Figure 2. The diagnoses were established prior to the administration of TRH on the basis of the clinical history, physical examination, and the results of other thyroid and/or pituitary function tests.

Among the normal euthyroid subjects, women and children were found to have higher levels of TSH at 30 minutes than men.

Among the patients with hyperthyroidism or primary (thyroidal), secondary (pituitary), or tertiary (hypothalamic) hypothyroidism, no significant differences in TSH levels by age or sex were found.

Figure 2

Normal: Baseline TSH levels of less than 10 microunits/mL (μU/mL) were observed in 97% of euthyroid normal subjects tested. Thirty minutes after TRH, the serum TSH increased by 2.0 mμU/mL or more in 95% of euthyroid subjects.

Hyperthyroidism: All hyperthyroid patients tested had baseline TSH levels of less than 10 μU/mL and a rise of less than 2 μU/pL 30 minutes after TRH.

Primary (thyroidal) hypothyroidism: The diagnosis of primary hypothyroidism is frequently supported by finding clearly elevated baseline TSH levels; 93% of patients tested had levels above 10 μU/mL. TRH administration to these patients generally would not be expected to yield additional useful information. Ninety-four percent of patients with primary hypothyroidism given ® TRH in clinical trials responded with a rise in TSH of 2.0 μU/mL or greater. Since this response is also found in normal subjects, TRH testing does not differentiate primary hypothyroidism from normal.

Secondary (pituitary) and tertiary (hypothalamic) hypothyroidism: In the presence of clinical and other laboratory evidence of hypothyroidism, the finding of a baseline TSH level less than 10 mU/mL should suggest secondary or tertiary hypothyroidism. In this situation, a response to TRH of less than 2 μU/mL suggests secondary hypothyroidism since this response was observed in about 60% of patients with, secondary hypothyroidism and only approximately 5% of patients with tertiary hypothyroidism. A TSH response to TRH greater than 2 μU/mL is not helpful in differentiating between secondary and tertiary hypothyroidism since this response was noted in about 40% of the former and about 95% of the latter.

Establishing the diagnosis of secondary or tertiary hypothyroidism requires a careful history and physical examination along with appropriate tests of anterior pituitary and/or target gland function. The TRH test should not be used as the only laboratory determinant for establishing these diagnoses.

Storage and Handling

Store at room temperature

PACKAGE LABEL.PRINCIPAL DISPLAY PANEL

Figure 3